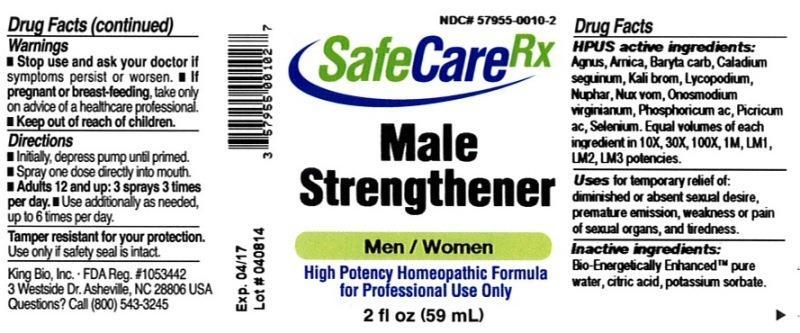 DRUG LABEL: Male Strengthener
NDC: 57955-0010 | Form: LIQUID
Manufacturer: King Bio Inc.
Category: homeopathic | Type: HUMAN OTC DRUG LABEL
Date: 20140421

ACTIVE INGREDIENTS: CHASTE TREE 10 [hp_X]/59 mL; ARNICA MONTANA 10 [hp_X]/59 mL; BARIUM CARBONATE 10 [hp_X]/59 mL; DIEFFENBACHIA SEGUINE 10 [hp_X]/59 mL; POTASSIUM BROMIDE 10 [hp_X]/59 mL; LYCOPODIUM CLAVATUM SPORE 10 [hp_X]/59 mL; NUPHAR LUTEUM ROOT 10 [hp_X]/59 mL; STRYCHNOS NUX-VOMICA SEED 10 [hp_X]/59 mL; ONOSMODIUM VIRGINIANUM WHOLE 10 [hp_X]/59 mL; PHOSPHORIC ACID 10 [hp_X]/59 mL; PICRIC ACID 10 [hp_X]/59 mL; SELENIUM 10 [hp_X]/59 mL
INACTIVE INGREDIENTS: WATER; CITRIC ACID MONOHYDRATE; POTASSIUM SORBATE

Male Strengthener™

ACTIVE INGREDIENT

Drug Facts__________________________________________________________________________________________________________

HPUS active ingredients: Agnus castus, Arnica montana, Baryta carbonica, Caladium seguinum, Kali bromatum, Lycopodium clavatum, Nuphar luteum, Nux vomica, Onosmodium virginianum, Phosphoricum acidum, Picnicum acidum, Selenium metallicum. Equal volumes of each ingredient in 10X, 30X, 100X, 1M, LM1, LM2, LM3 potencies.

INDICATIONS AND USAGE

Uses for temporary relief of: diminished or absent sexual desire, premature emission, weakness or pain of sexual organs, and tiredness .

Inactive Ingredients:

Bio-Energetically Enhanced™ pure water, citric acid and potassium sorbate.

Warnings

- Stop use and ask your doctor if symptoms persist or worsen.
- If pregnant or breast-feeding, take only on advice of a healthcare professional.

- Keep out of reach of children.

Directions

- Initially, depress pump until primed.
- Spray one dose directly into mouth.
- Adults 12 and up: 3 sprays 3 times per day.
- Use additionally as needed, up to 6 times per day.

OTHER SAFETY INFORMATION

Tamper resistant for your protection. Use only if safety seal is intact.

PURPOSE

Uses for temporary relief of:

- diminished or absent sexual desire
- premature emission
- weakness or pain of sexual organs
- tiredness